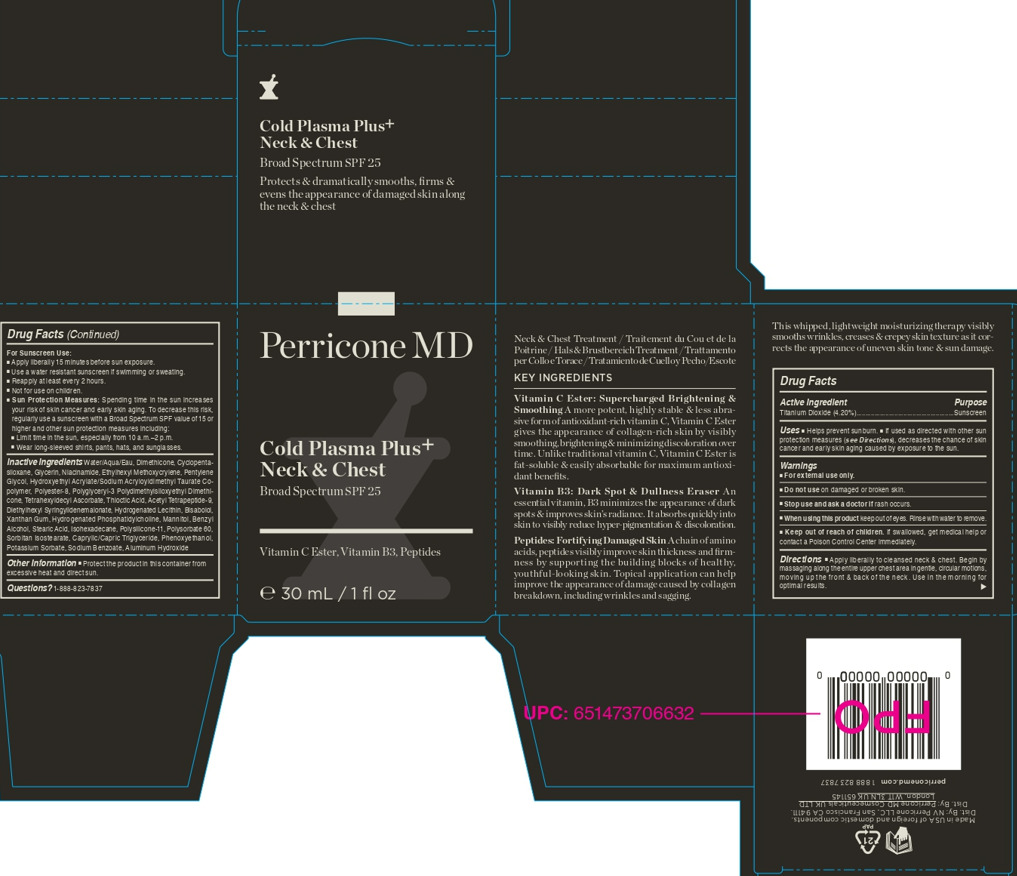 DRUG LABEL: Cold Plasma Plus Neck and Chest SPF25
NDC: 45634-167 | Form: CREAM
Manufacturer: NV Perricone LLC
Category: otc | Type: HUMAN OTC DRUG LABEL
Date: 20230905

ACTIVE INGREDIENTS: TITANIUM DIOXIDE 1.26 g/30 g
INACTIVE INGREDIENTS: WATER; HYDROXYETHYL ACRYLATE/SODIUM ACRYLOYLDIMETHYL TAURATE COPOLYMER (45000 MPA.S AT 1%); DIETHYLHEXYL SYRINGYLIDENEMALONATE; .ALPHA.-BISABOLOL, (+/-)-; NIACINAMIDE; POLYESTER-8 (1400 MW, CYANODIPHENYLPROPENOYL CAPPED); HYDROGENATED SOYBEAN PHOSPHATIDYLCHOLINE; GLYCERIN; DIMETHICONE CROSSPOLYMER (450000 MPA.S AT 12% IN CYCLOPENTASILOXANE); PENTYLENE GLYCOL; POLYGLYCERYL-3 POLYDIMETHYLSILOXYETHYL DIMETHICONE (4000 MPA.S); ETHYLHEXYL METHOXYCRYLENE; ACETYL TETRAPEPTIDE-9; DIMETHICONE; BENZYL ALCOHOL; ISOHEXADECANE; POLYSORBATE 60; TETRAHEXYLDECYL ASCORBATE; POTASSIUM SORBATE; XANTHAN GUM; STEARIC ACID; ALUMINUM HYDROXIDE; HYDROGENATED SOYBEAN LECITHIN; MANNITOL; POLYSILICONE-15; PHENOXYETHANOL; SORBITAN ISOSTEARATE; SODIUM BENZOATE; MEDIUM-CHAIN TRIGLYCERIDES; THIOCTIC ACID

INACTIVE INGREDIENT

-651145_CPPP_Neck_1oz_Jar_FC_US_v05_page-0001.jpg

KEEP OUT OF REACH OF CHILDREN

-651145_CPPP_Neck_1oz_Jar_FC_US_v05_page-0001.jpg

PURPOSE

-651145_CPPP_Neck_1oz_Jar_FC_US_v05_page-0001.jpg

ACTIVE INGREDIENT

-651145_CPPP_Neck_1oz_Jar_FC_US_v05_page-0001.jpg

INDICATIONS AND USAGE

-651145_CPPP_Neck_1oz_Jar_FC_US_v05_page-0001.jpg

DOSAGE AND ADMINISTRATION

-651145_CPPP_Neck_1oz_Jar_FC_US_v05_page-0001.jpg